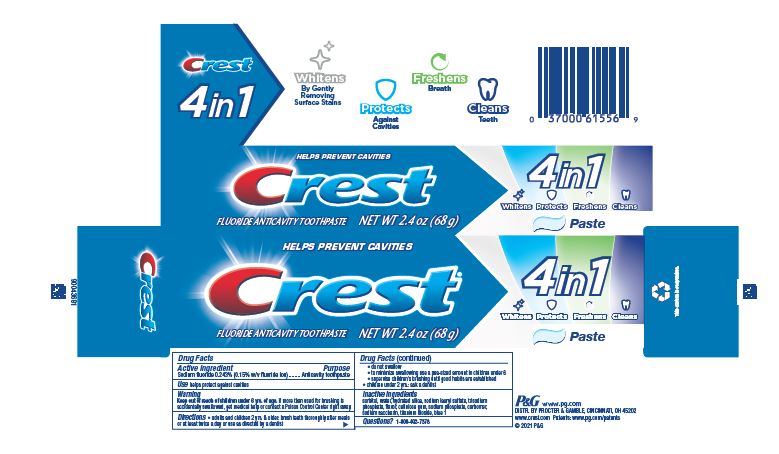 DRUG LABEL: Crest
NDC: 69423-852 | Form: PASTE, DENTIFRICE
Manufacturer: The Procter & Gamble Manufacturing Company
Category: otc | Type: HUMAN OTC DRUG LABEL
Date: 20250731

ACTIVE INGREDIENTS: SODIUM FLUORIDE 1.5 mg/1 g
INACTIVE INGREDIENTS: SODIUM PHOSPHATE; TITANIUM DIOXIDE; FD&C BLUE NO. 1; SACCHARIN SODIUM; CARBOXYMETHYLCELLULOSE SODIUM, UNSPECIFIED FORM; SORBITOL; WATER; HYDRATED SILICA; CARBOXYPOLYMETHYLENE; SODIUM PHOSPHATE, TRIBASIC, ANHYDROUS; SODIUM LAURYL SULFATE

Crest 4in1

Drug Facts

Active ingredient

Sodium fluoride 0.243% (0.15% w/v fluoride ion)

Purpose

Anticavity toothpaste

Use

helps protect against cavities

Warnings

Keep out of reach of children under 6 yrs. of age. If more than used for brushing is accidentally swallowed, get medical help or contact a Poison Control Center right away.

Directions

- adults and children 2 yrs. & older: brush teeth thoroughly after meals or at least twice a day or use as directed by a dentist
  - do not swallow
  - to minimize swallowing use a pea-sized amount in children under 6
  - supervise children's brushing until good habits are established
- children under 2 yrs.: ask a dentist

Inactive ingredients

sorbitol, water, hydrated silica, sodium lauryl sulfate, trisodium phosphate, flavor, cellulose gum, sodium phosphate, carbomer, sodium saccharin, titanium dioxide, blue 1

Questions?

1-800-492-7378

Dist. by Procter & Gamble, Cincinnati OH 45202

PRINCIPAL DISPLAY PANEL - 68 g Carton

HELPS PREVENT CAVITIES

Crest

FLUORIDE ANTICAVITY TOOTHPASTE

NET WT 2.4 OZ (68 g)

4in1

Whitens

Protects

Freshens

Cleans

Paste